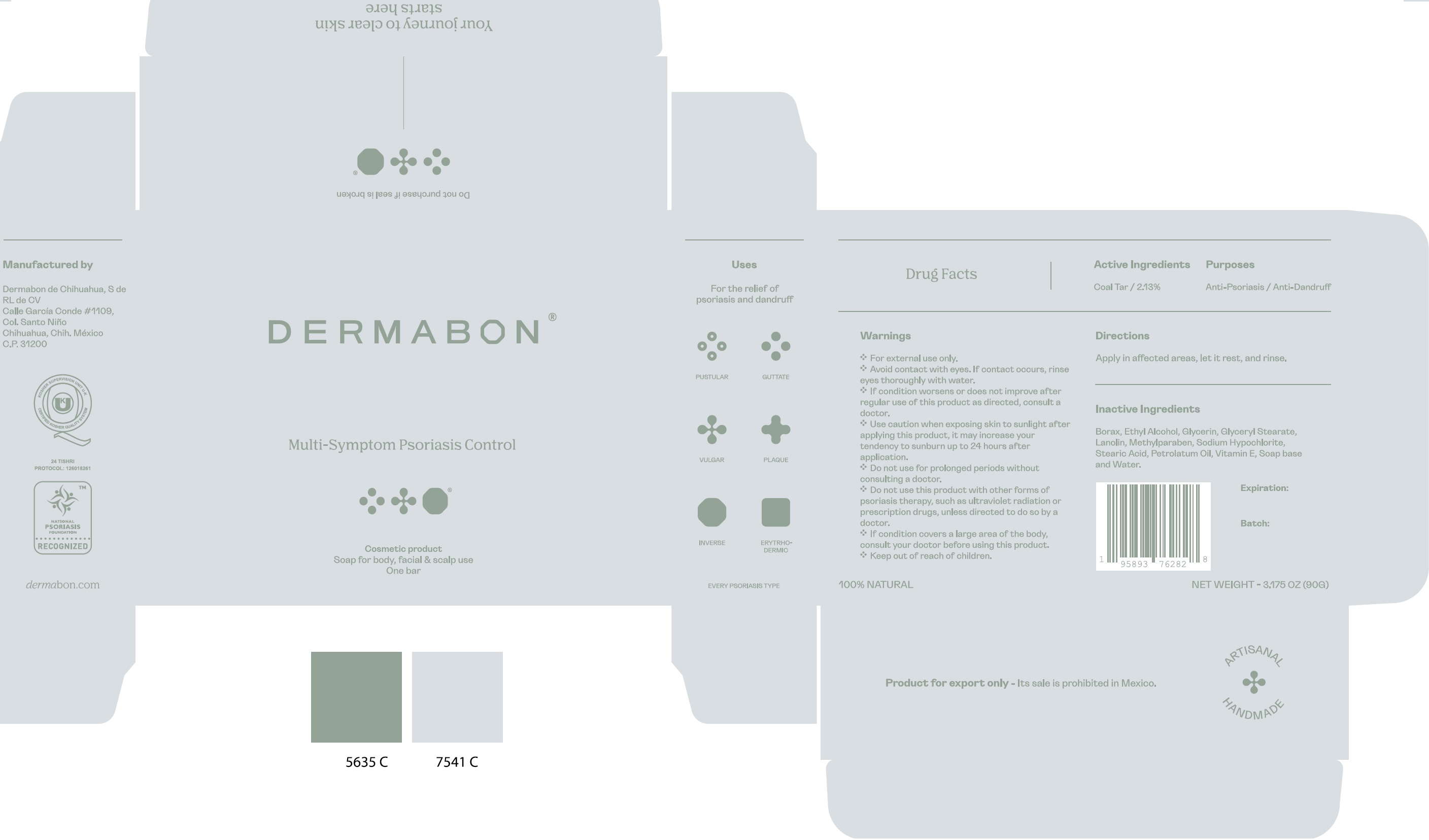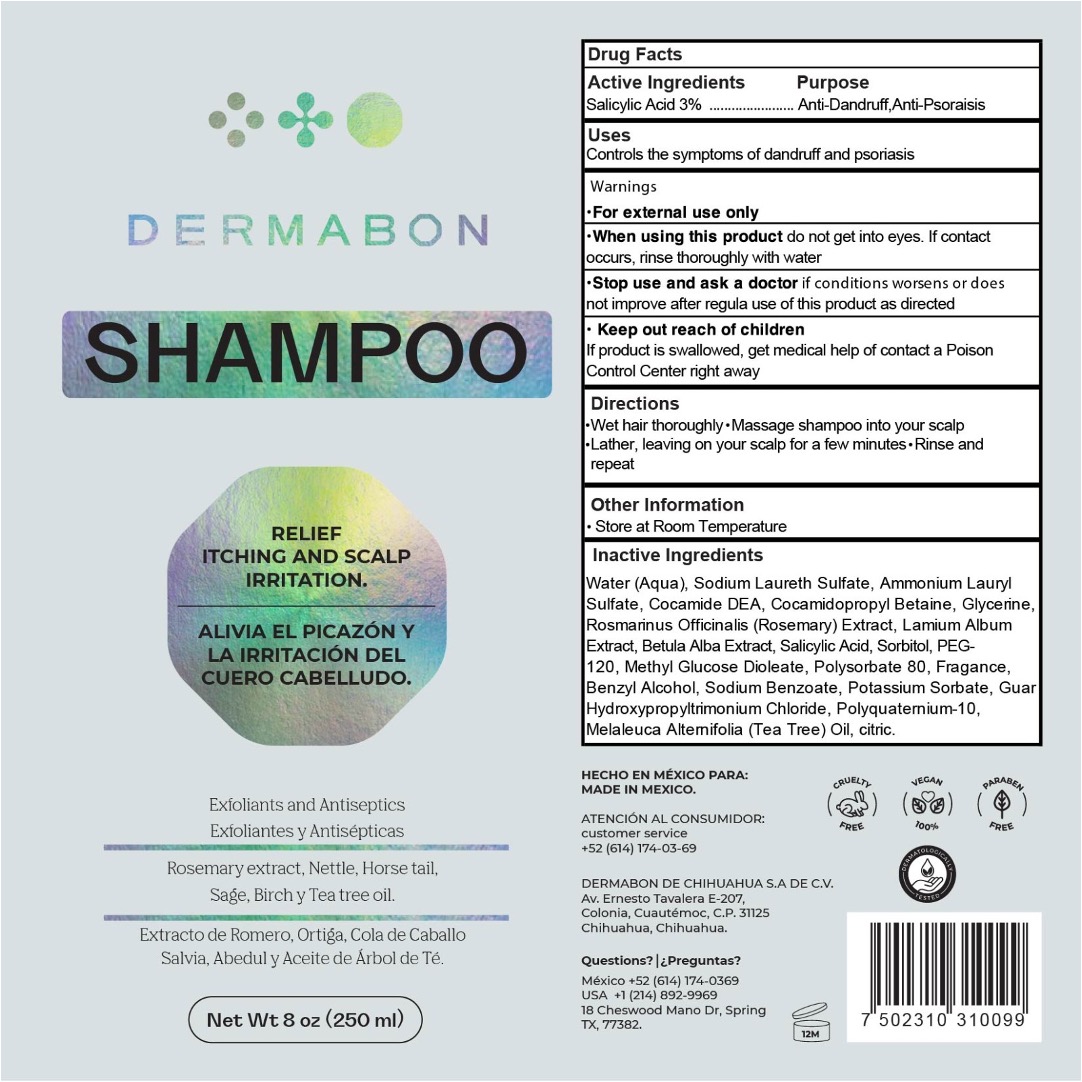 DRUG LABEL: Dermabon Multi Symptom Psoriasis Control
NDC: 49758-001 | Form: SOAP
Manufacturer: Dermabon de Chihuahua, S.A. de C.V.
Category: otc | Type: HUMAN OTC DRUG LABEL
Date: 20250701

ACTIVE INGREDIENTS: COAL TAR 21.3 mg/1 g
INACTIVE INGREDIENTS: SODIUM BORATE; ALCOHOL; GLYCERIN; GLYCERYL MONOSTEARATE; LANOLIN; METHYLPARABEN; SODIUM HYPOCHLORITE; STEARIC ACID; .ALPHA.-TOCOPHEROL; WATER

Dermabon Multi-Symptom Psoriasis Control Soap

Active Ingredients

Coal Tar / 2.13%

Purposes

Anti-Psoriasis / Anti-Dandruff

Uses

For the relief of psoriasis and dandruff

Warnings

- For external use only.
- Avoid contact with eyes. If contact occurs, rinse eyes thoroughly with water.
- If condition worsens or does not improve after regular use of this product as directed, consult a doctor.
- Use caution when exposing skin to sunlight after applying this product, it may increase your tendency to sunburn up to 24 hours after application.

Do not use

- for prolonged periods without consulting a doctor.
- do not use this proudct with other forms of psoriasis therapy, such as ultraviolet radiation or prescription drugs, unless directed to do so by a doctor.
- If condition covers a large area of the body, consult your doctor before using this product.

Directions

Apply in affected areas, let it rest, and rinse.

Inactive Ingredients

Borax, Ethyl Alcohol, Glycerin, Glyceryl Stearate, Lanolin, Methylparaben, Sodium Hypoochlorite, Stearic Acid, Petrolatum Oil, Vitamin E, Soap base and Water.